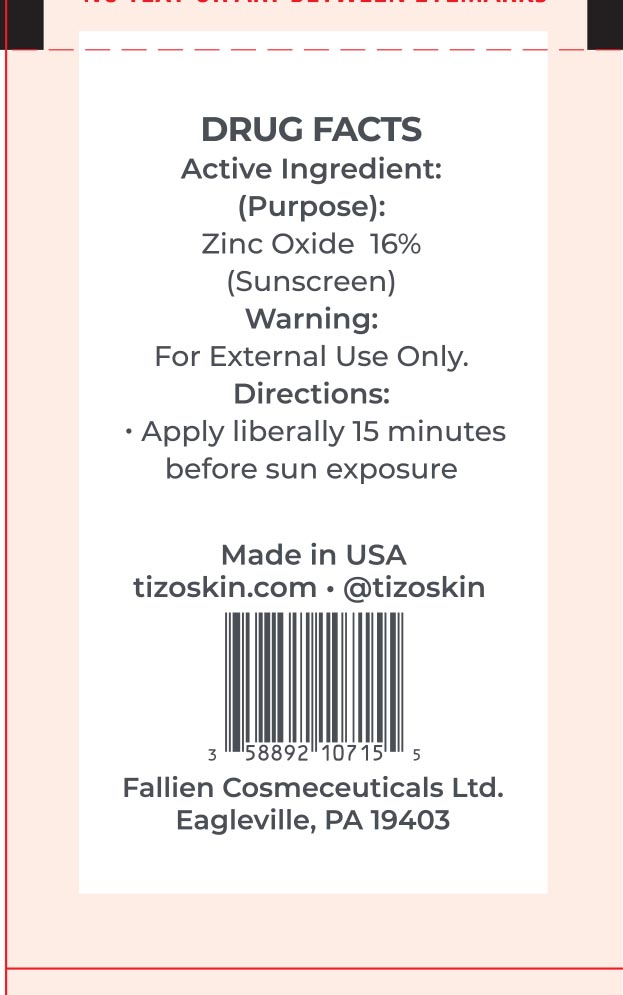 DRUG LABEL: TiZO Photoceutical AM Replenish - Tinted
NDC: 58892-101 | Form: CREAM
Manufacturer: Fallien Cosmeceuticals, LTD
Category: otc | Type: HUMAN OTC DRUG LABEL
Date: 20250128

ACTIVE INGREDIENTS: ZINC OXIDE 160 mg/1 g
INACTIVE INGREDIENTS: POLYHYDROXYSTEARIC ACID (2300 MW); VINYL DIMETHICONE/METHICONE SILSESQUIOXANE CROSSPOLYMER; DIMETHICONE CROSSPOLYMER; IRON OXIDES; TETRAHEXYLDECYL ASCORBATE; CERAMIDE 3; PEG-10 DIMETHICONE (600 CST); CAPRYLIC/CAPRIC TRIGLYCERIDE; DIMETHICONE; DIMETHICONE/VINYL DIMETHICONE CROSSPOLYMER (SOFT PARTICLE); CYCLOPENTASILOXANE; CYCLOHEXASILOXANE; ALPHA-TOCOPHEROL ACETATE; DIMETHICONOL (2000 CST); HYDROGEN DIMETHICONE (20 CST)

Actve Ingredient:

Zinc Oxide 16%

(Purpose)

Sunscreen

Directions:

Apply liberally 15 minutes before sun exposure.

Warning:

For external use only.

Warning and DIrections:

For external use only. Aplly liberally 15 minutes before sun exposure.

INACTIVE INGREDIENT

Capric/Caprylic Triglyceride, Ceramide 3, Cyclohexasiloxane, Cyclopentasiloxane, Dimethicone, Dimethicone Crosspolymer, Dimethicone/Vinyl Dimethicone Crosspolymer, Dimethiconol, Iron Oxide, Hydrogen Dimethicone, PEG-10 Dimethicone, Polyhydroxystearic Acid, Tetrahexyldecyl Ascorbate, Tocopheryl Acetate, Vinyl Dimethicone/Methicone Silsesquioxane Crosspolymer